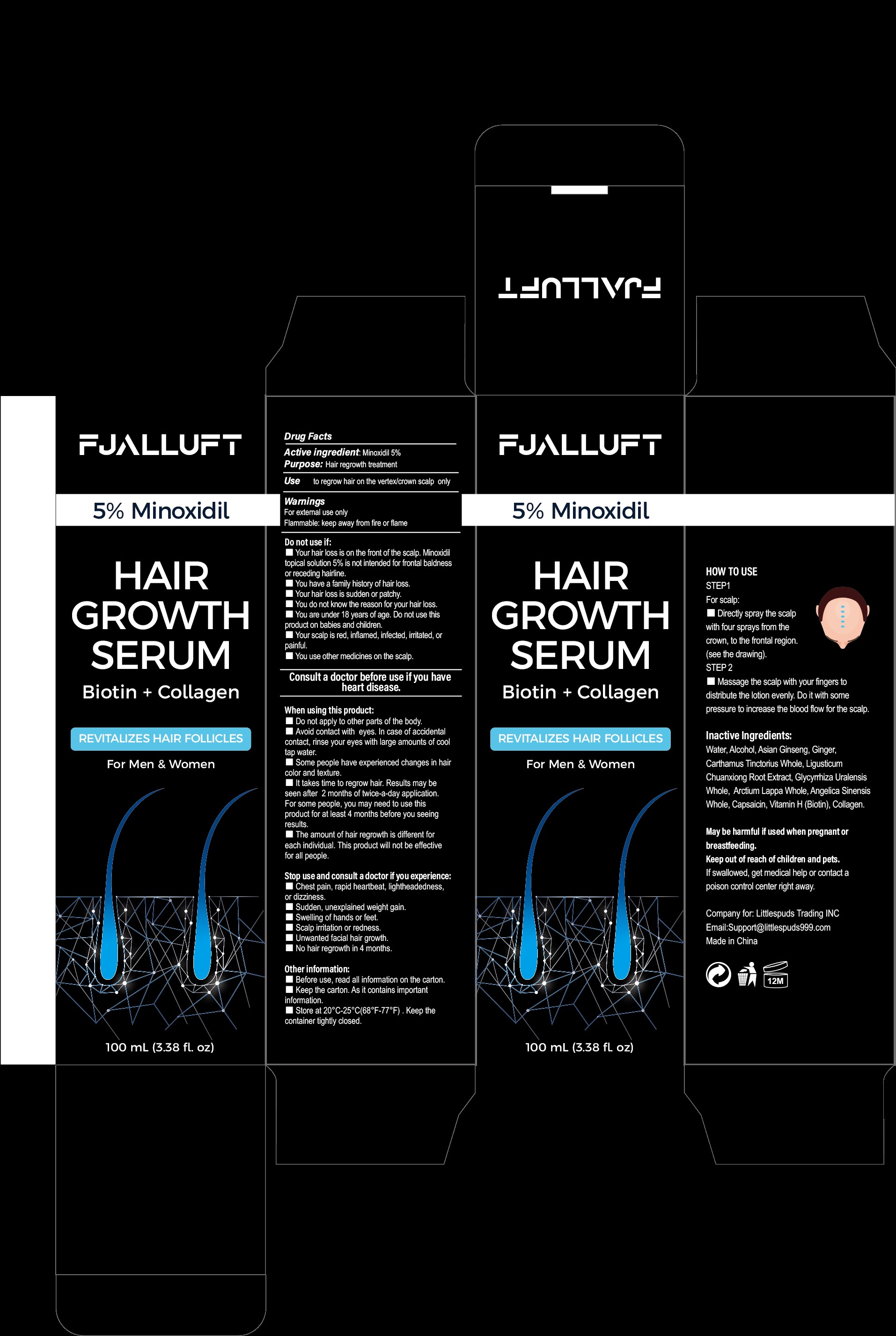 DRUG LABEL: Hair Growth Serum
NDC: 83563-001 | Form: SPRAY
Manufacturer: Fujian Oumao Electronic Commerce Co. , Ltd.
Category: otc | Type: HUMAN OTC DRUG LABEL
Date: 20231019

ACTIVE INGREDIENTS: MINOXIDIL 5 g/100 mL
INACTIVE INGREDIENTS: WATER; ALCOHOL

ACTIVE INGREDIENT

有效成分：米诺地尔5%

KEEP OUT OF REACH OF CHILDREN

放在儿童和宠物接触不到的地方。

PURPOSE

头发再生治疗